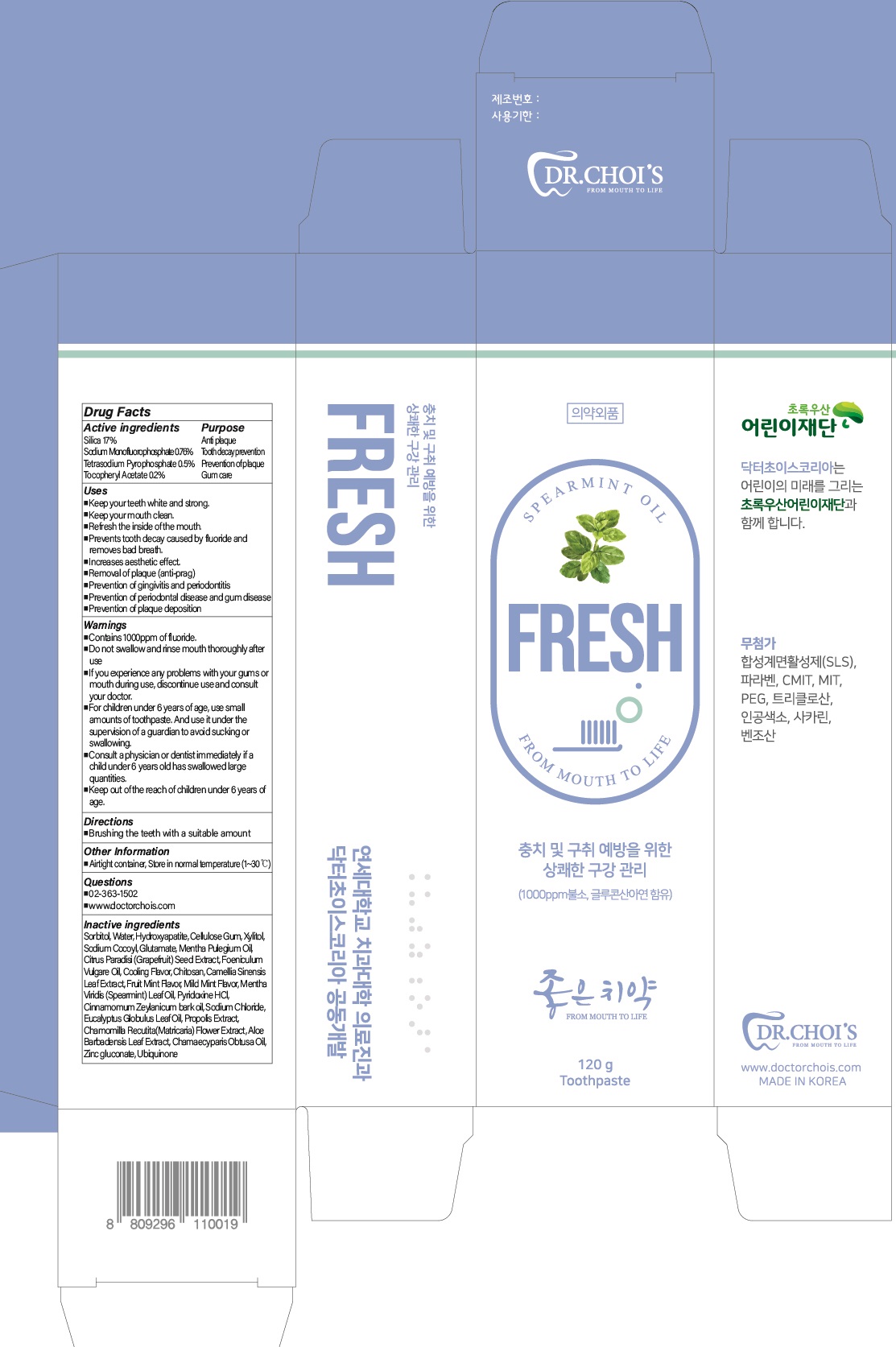 DRUG LABEL: DR.CHOIS TOOTHPASTE FRESH
NDC: 73666-0520 | Form: PASTE, DENTIFRICE
Manufacturer: Doctor Choi`s Korea Co., LTD.
Category: otc | Type: HUMAN OTC DRUG LABEL
Date: 20220920

ACTIVE INGREDIENTS: SILICON DIOXIDE 17.0 g/100 g; Sodium Monofluorophosphate 0.76 g/100 g; SODIUM PYROPHOSPHATE 0.5 g/100 g; .ALPHA.-TOCOPHEROL ACETATE 0.2 g/100 g
INACTIVE INGREDIENTS: Sorbitol; Water; TRIBASIC CALCIUM PHOSPHATE

ACTIVE INGREDIENTS

Silica 17%
Sodium Monofluorophosphate 0.76%
Tetrasodium Pyrophosphate 0.5%
Tocopheryl Acetate 0.2%

PURPOSE

Anti plaque
Tooth decay prevention
Prevention of plaque
Gum care

Uses

■ Keep your teeth white and strong.
■ Keep your mouth clean.
■ Refresh the inside of the mouth.
■ Prevents tooth decay caused by fluoride and removes bad breath.
■ Increases aesthetic effect.
■ Removal of plaque (anti-prag)
■ Prevention of gingivitis and periodontitis
■ Prevention of periodontal disease and gum disease
■ Prevention of plaque deposition

WARNINGS

■ Contains 1000ppm of fluoride.
■ Do not swallow and rinse mouth thoroughly after use
■ If you experience any problems with your gums or mouth during use,
discontinue use and consult your doctor.
■ For children under 6 years of age, use small amounts of toothpaste. And use it
under the supervision of a guardian to avoid sucking or swallowing.
■ Consult a physician or dentist immediately if a child under 6 years old has
swallowed large quantities.
■ Keep out of the reach of children under 6 years of age.

KEEP OUT OF REACH OF CHILDREN

■ Keep out of the reach of children under 6 years of age.

Directions

■ Brushing the teeth with a suitable amount

Other Information

■ Airtight container, Store in normal temperature (1~30℃)

Questions

■ 02-363-1502
■ www.doctorchois.com

INACTIVE INGREDIENTS

Sorbitol, Water, Hydroxyapatite, Cellulose Gum, Xylitol, Sodium Cocoyl, Glutamate, Mentha Pulegium Oil, Citrus Paradisi (Grapefruit) Seed Extract, Foeniculum Vulgare Oil, Cooling Flavor, Chitosan, Camellia Sinensis Leaf Extract, Fruit Mint Flavor, Mild Mint Flavor, Mentha Viridis (Spearmint) Leaf Oil, Pyridoxine HCl, Cinnamomum Zeylanicum bark oil, Sodium Chloride, Eucalyptus Globulus Leaf Oil, Propolis Extract, Chamomilla Recutita(Matricaria) Flower Extract, Aloe Barbadensis Leaf Extract, Chamaecyparis Obtusa Oil, Zinc gluconate, Ubiquinone